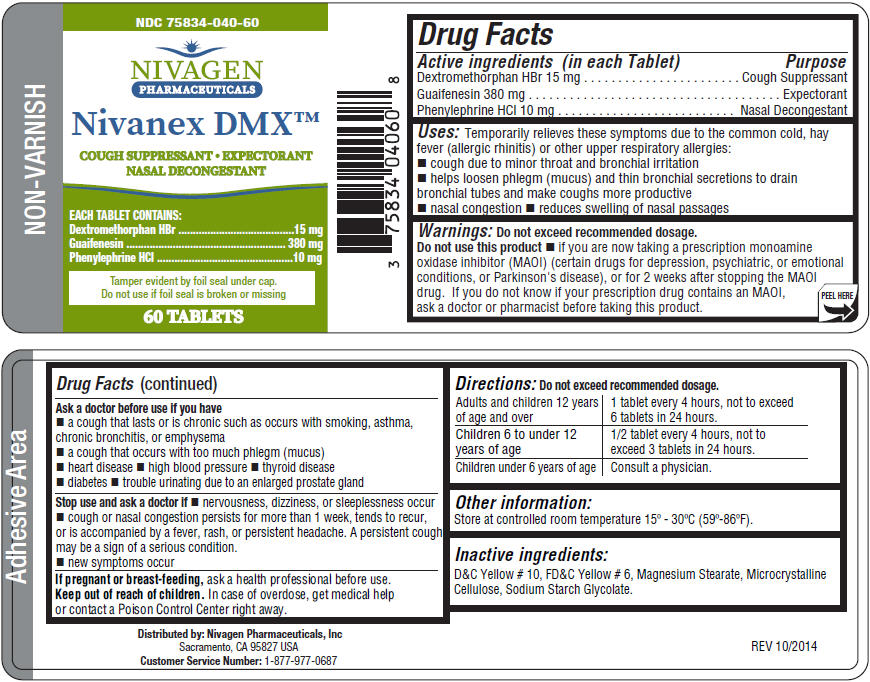 DRUG LABEL: Nivanex DMX
NDC: 75834-040 | Form: TABLET
Manufacturer: Nivagen Pharmaceuticals, Inc.
Category: otc | Type: HUMAN OTC DRUG LABEL
Date: 20220214

ACTIVE INGREDIENTS: GUAIFENESIN 380 mg/1 1; DEXTROMETHORPHAN HYDROBROMIDE 15 mg/1 1; PHENYLEPHRINE HYDROCHLORIDE 10 mg/1 1
INACTIVE INGREDIENTS: D&C YELLOW NO. 10; FD&C YELLOW NO. 6; MAGNESIUM STEARATE; MICROCRYSTALLINE CELLULOSE

Nivanex DMX™

Drug Facts

ACTIVE INGREDIENT

Active ingredients (in each Tablet) | Purpose
Dextromethorphan HBr 15 mg | Cough Suppressant
Guaifenesin 380 mg | Expectorant
Phenylephrine HCl 10 mg | Nasal Decongestant

Uses

Temporarily relieves these symptoms due to the common cold, hay fever (allergic rhinitis) or other upper respiratory allergies:

- cough due to minor throat and bronchial irritation
- helps loosen phlegm (mucus) and thin bronchial secretions to drain bronchial tubes and make coughs more productive
- nasal congestion
- reduces swelling of nasal passages

Warnings

Do not exceed recommended dosage.

Do not use this product

- if you are now taking a prescription monoamine oxidase inhibitor (MAOI) (certain drugs for depression, psychiatric, or emotional conditions, or Parkinson's disease), or for 2 weeks after stopping the MAOI drug. If you do not know if your prescription drug contains an MAOI, ask a doctor or pharmacist before taking this product.

Ask a doctor before use if you have

- a cough that lasts or is chronic such as occurs with smoking, asthma, chronic bronchitis, or emphysema
- a cough that occurs with too much phlegm (mucus)
- heart disease
- high blood pressure
- thyroid disease
- diabetes
- trouble urinating due to an enlarged prostate gland

Stop use and ask a doctor if

- nervousness, dizziness, or sleeplessness occur
- cough or nasal congestion persists for more than 1 week, tends to recur, or is accompanied by a fever, rash, or persistent headache. A persistent cough may be a sign of a serious condition.
- new symptoms occur

PREGNANCY OR BREAST FEEDING

If pregnant or breast-feeding, ask a health professional before use.

Keep out of reach of children. In case of overdose, get medical help or contact a Poison Control Center right away.

Directions

Do not exceed recommended dosage.

Adults and children 12 years of age and over | 1 tablet every 4 hours, not to exceed 6 tablets in 24 hours.
Children 6 to under 12 years of age | 1/2 tablet every 4 hours, not to exceed 3 tablets in 24 hours.
Children under 6 years of age | Consult a physician.

Other information

Store at controlled room temperature 15º - 30ºC (59º-86ºF).

Inactive ingredients

D&C Yellow # 10, FD&C Yellow # 6, Magnesium Stearate, Microcrystalline Cellulose, Sodium Starch Glycolate.

Distributed by: Nivagen Pharmaceuticals, Inc
Sacramento, CA 95827 USA
Customer Service Number: 1-877-977-0687

PRINCIPAL DISPLAY PANEL - 60 Tablet Bottle Label

NDC 75834-040-60

NIVAGEN
PHARMACEUTICALS

Nivanex DMX™

COUGH SUPPRESSANT • EXPECTORANT
NASAL DECONGESTANT

EACH TABLET CONTAINS:
Dextromethorphan HBr
15 mg
Guaifenesin
380 mg
Phenylephrine HCl
10 mg

Tamper evident by foil seal under cap.
Do not use if foil seal is broken or missing

60 TABLETS